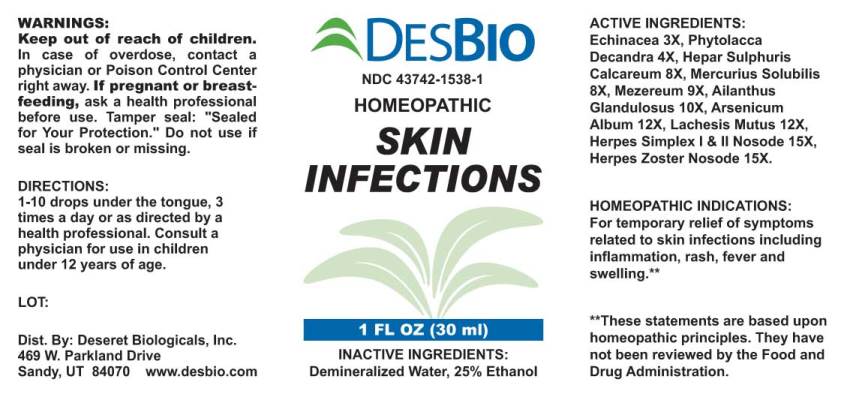 DRUG LABEL: Skin Infections
NDC: 43742-1538 | Form: LIQUID
Manufacturer: Deseret Biologials, Inc.
Category: homeopathic | Type: HUMAN OTC DRUG LABEL
Date: 20240202

ACTIVE INGREDIENTS: ECHINACEA ANGUSTIFOLIA 3 [hp_X]/1 mL; PHYTOLACCA AMERICANA ROOT 4 [hp_X]/1 mL; CALCIUM SULFIDE 8 [hp_X]/1 mL; MERCURIUS SOLUBILIS 8 [hp_X]/1 mL; DAPHNE MEZEREUM BARK 9 [hp_X]/1 mL; AILANTHUS ALTISSIMA FLOWERING TWIG 10 [hp_X]/1 mL; ARSENIC TRIOXIDE 12 [hp_X]/1 mL; LACHESIS MUTA VENOM 12 [hp_X]/1 mL; HUMAN HERPESVIRUS 1 15 [hp_X]/1 mL; HUMAN HERPESVIRUS 2 15 [hp_X]/1 mL; HUMAN HERPESVIRUS 3 15 [hp_X]/1 mL
INACTIVE INGREDIENTS: WATER; ALCOHOL

Drug Facts:

ACTIVE INGREDIENTS:

Echinacea (Angustifolia) 3X, Phytolacca Decandra 4X, Hepar Sulphuris Calcareum 8X, Mercurius Solubilis 8X, Mezereum 9X, Ailanthus Glandulosus 10X, Arsenicum Album 12X, Lachesis Mutus 12X, Herpes Simplex I & II Nosode 15X, Herpes Zoster Nosode 15X.

HOMEOPATHIC INDICATIONS:

For temporary relief of symptoms related to skin infections including inflammation, rash, fever and swelling.**

**These statements are based upon homeopathic principles. They have not been reviewed by the Food and Drug Administration.

WARNINGS:

Keep out of reach of children. In case of overdose, contact physician or Poison Control Center right away.

If pregnant or breast-feeding, seek advice of a health professional before use.

Tamper seal: "Sealed for Your Protection." Do not use if seal is broken or missing.

Keep out of reach of children. In case of overdose, contact physician or Poison Control Center right away.

DIRECTIONS:

1-10 drops under the tongue, 3 times a day or as directed by a health professional. Consult a physician for use in children under 12 years of age.

HOMEOPATHIC INDICATIONS:

For temporary relief of symptoms related to skin infections including inflammation, rash, fever and swelling.**

**These statements are based upon homeopathic principles. They have not been reviewed by the Food and Drug Administration.

INACTIVE INGREDIENTS:

Demineralized Water, 25% Ethanol.

QUESTIONS:

Dist. By: Deseret Biologicals, Inc.

469 W. Parkland Drive

Sandy, UT 84070 www.desbio.com

PACKAGE LABEL DISPLAY:

DESBIO

NDC 43742-0171-1

HOMEOPATHIC

SKIN

INFECTIONS

1 FL OZ (30 ml)